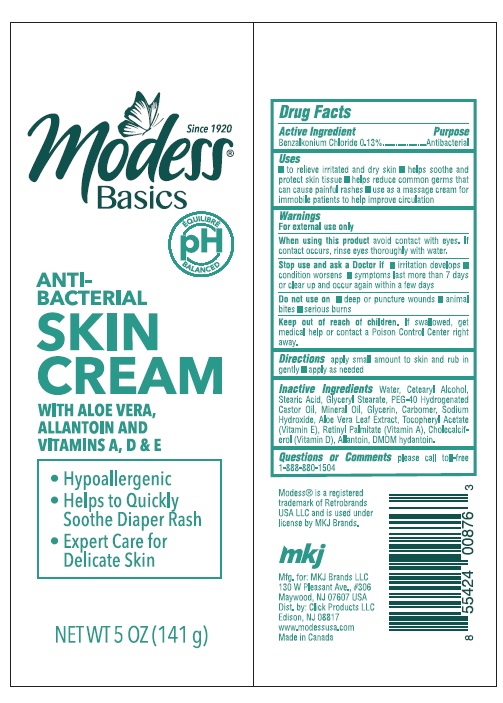 DRUG LABEL: Antibacterial
NDC: 71611-079 | Form: CREAM
Manufacturer: CLICK PRODUCTS LLC
Category: otc | Type: HUMAN OTC DRUG LABEL
Date: 20210722

ACTIVE INGREDIENTS: BENZALKONIUM CHLORIDE 1.3 mg/1 mL
INACTIVE INGREDIENTS: WATER; CETOSTEARYL ALCOHOL; STEARIC ACID; GLYCERYL STEARATE SE; POLYOXYL 40 HYDROGENATED CASTOR OIL; GLYCERIN; ALLANTOIN; MINERAL OIL; SODIUM HYDROXIDE; ALOE VERA LEAF; .ALPHA.-TOCOPHEROL ACETATE; VITAMIN A; CHOLECALCIFEROL; DMDM HYDANTOIN

Antibacterial Skin Cream with Aloe Vera, Allantoin and Vitamins A,D & E

ACTIVE INGREDIENT

Benzalkonium Chloride - 0.13%

Purpose - Antibacterial

INDICATIONS AND USAGE

-to relieve irritated and dry skin

-helps soothe and protect skin tissue

-helps reduce common germs that can cause painful rashes

-use as a massage cream for immobile patients to help improve circulation

Warnings For external use only

Avoid contact with eyes, if contact occurs, rinse eyes thoroughly with water

Stop use and ask a doctor if irritation or redness develops

condition worsens

symptoms last more than 7 days or clear up and occur again within a few days

When using this product

Avoid contact with eyes.In case of contact, flush and rinse with water.

Remove contact lenses, if present and easy to do. Continue rinsing.

Keep out of reach of children

Except under adult supervision. DO NOT EAT DRINK.

Keep away from food,drink and animal feeding stuffs,

If swallowed get medical help or contact posion control right away.

Directions

apply small amount to skin and rub in gently, apply as needed

INACTIVE INGREDIENT

Water, cetearyl alcohol, stearic acid, glyceryl stearate, PEG-40 hydrogenated castor oil, mineral oil, glycerin, carbomer, sodium hydroxide, aloe vera leaf extract, tocopheryl acetate, Vitamin A, Vitamin D, allantoin, DMDM hydantoin